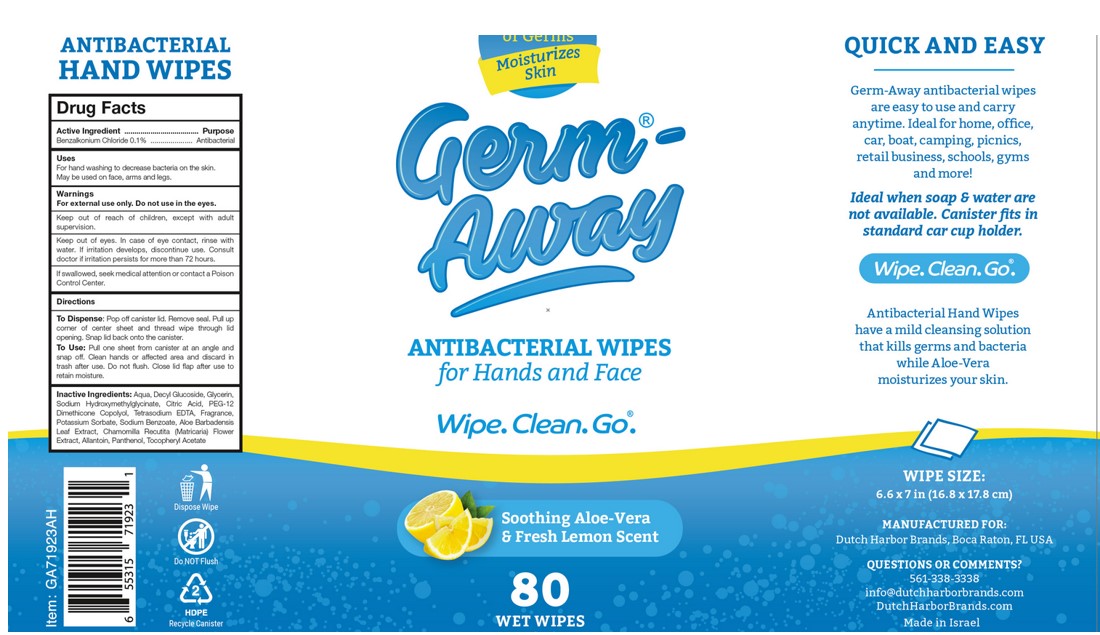 DRUG LABEL: Germ-Away
NDC: 74680-107 | Form: CLOTH
Manufacturer: Unico International Trading Corp
Category: otc | Type: HUMAN OTC DRUG LABEL
Date: 20260108

ACTIVE INGREDIENTS: BENZALKONIUM CHLORIDE 1 mg/1 g
INACTIVE INGREDIENTS: 3,7-DIMETHYL-1-OCTANOL; DIPHENYL ETHER; CP FORMATE; DECYL GLUCOSIDE; SODIUM BENZOATE; GLYCERIN; PANTHENOL; TETRAHYDROLINALOOL; 2,2'-OXYDIPROPANOL; EUCALYPTOL; SODIUM HYDROXYMETHYLGLYCINATE; CHAMOMILE; ALOE VERA LEAF; POTASSIUM SORBATE; EDETATE SODIUM; COUMARIN; ALLANTOIN; ANHYDROUS CITRIC ACID; WATER; PEG-12 DIMETHICONE (300 CST); .ALPHA.-TOCOPHEROL ACETATE

Germ-Away

Active Ingredient

Benzalkonium Chloride 0.1%

Keep out of the reach of children.

Keep out of reach of children, except with adult supervision.

Warnings

For external use only. Do not use in the eyes.

Keep out of eyes. In case of eye contact, rinse with water. If irritation develops, discontinue use. Consult doctor if irritation persists for more than 72 hours.

If swallowed, seek medical attention or contact a Poison Control Center.

To dispense

Pop off canister lid. Remove seal. Pull up corner of center sheet and thread wipe through lid opening. Snap lid back onto the canister.

To Use: Pull one sheet from canister at an angle and snap off. Clean hands or affected area and discard in trash after use. Do not flush. Close lid flap after use to retain moisture.

Purpose

Anti-bacterial

Directions

Pull one sheet from canister at an angle. Sanitize hands or other affected area. Discard in trash after use. Do not flush. Close lid flap after use to retain moisture.

Inactive Ingredients

Aqua, Decyl Glucoside, Glycerin, Sodium Hydroxymethylglycinate, Citric Acid, PEG-12 Dimethicone Copolyol, Tetrasodium EDTA, Potassium Sorbate, Sodium Benzoate, Aloe Barbadensis Leaf Extract, Chamomilla Recutita (Matricaria) Flower Extract, Allantoin, Panthenol, Tocopheryl Acetate, fragrance